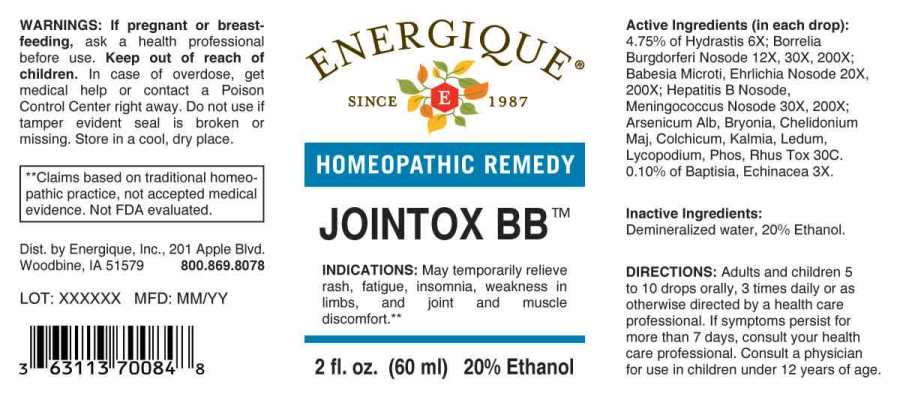 DRUG LABEL: Jointox BB
NDC: 44911-0642 | Form: LIQUID
Manufacturer: Energique, Inc.
Category: otc | Type: HUMAN OTC DRUG LABEL
Date: 20250519

ACTIVE INGREDIENTS: BAPTISIA TINCTORIA ROOT 3 [hp_X]/1 mL; ECHINACEA ANGUSTIFOLIA WHOLE 3 [hp_X]/1 mL; GOLDENSEAL 6 [hp_X]/1 mL; BORRELIA BURGDORFERI 12 [hp_X]/1 mL; BABESIA MICROTI 20 [hp_X]/1 mL; EHRLICHIA CANIS 20 [hp_X]/1 mL; NEISSERIA MENINGITIDIS 30 [hp_X]/1 mL; HEPATITIS B VIRUS 30 [hp_X]/1 mL; ARSENIC TRIOXIDE 30 [hp_C]/1 mL; BRYONIA ALBA ROOT 30 [hp_C]/1 mL; CHELIDONIUM MAJUS WHOLE 30 [hp_C]/1 mL; COLCHICUM AUTUMNALE BULB 30 [hp_C]/1 mL; KALMIA LATIFOLIA LEAF 30 [hp_C]/1 mL; LEDUM PALUSTRE TWIG 30 [hp_C]/1 mL; LYCOPODIUM CLAVATUM SPORE 30 [hp_C]/1 mL; PHOSPHORUS 30 [hp_C]/1 mL; TOXICODENDRON PUBESCENS LEAF 30 [hp_C]/1 mL
INACTIVE INGREDIENTS: WATER; ALCOHOL

DRUG FACTS:

ACTIVE INGREDIENTS:

(in each drop): 4.75% of Hydrastis Canadensis 6X; Borrelia Burgdorferi Nosode 12X, 30X, 200X; Babesia Microti 20X, 200X, Ehrlichia Nosode (Canine) 20X, 200X; Hepatitis B Nosode 30X, 200X, Meningococcus Nosode 30X, 200X; Arsenicum Album 30C, Bryonia (Alba) 30C, Chelidonium Majus 30C, Colchicum Autumnale 30C, Kalmia Latifolia 30C, Ledum Palustre 30C, Lycopodium Clavatum 30C, Phosphorus 30C, Rhus Tox 30C. 0.10% of Baptisia Tinctoria 3X, Echinacea (Angustifolia) 3X.

INDICATIONS:

May temporarily relieve rash, fatigue, insomnia, weakness in limbs, and joint and muscle discomfort**

**Claims based on traditional homeopathic practice, not accepted medical evidence. Not FDA evaluated.

WARNINGS:

If pregnant or breastfeeding, ask a health professional before use.

Keep out of reach of children. In case of overdose, get medical help or contact a Poison Control Center right away.

Do not use if tamper evident seal is broken or missing.

Store in a cool, dry place.

Keep out of reach of children. In case of overdose, get medical help or contact a Poison Control Center right away.

DIRECTIONS:

Adults and children 5 to 10 drops orally, 3 times daily or as otherwise directed by a health care professional. If symptoms persist for more than 7 days, consult your health care professional. Consult a physician for use in children under 12 years of age.

INDICATIONS:

May temporarily relieve rash, fatigue, insomnia, weakness in limbs, and joint and muscle discomfort**

**Claims based on traditional homeopathic practice, not accepted medical evidence. Not FDA evaluated.

INACTIVE INGREDIENTS:

Demineralized water, 20% Ethanol.

QUESTIONS:

Dist. by Energique, Inc.

201 Apple Blvd.

Woodbine, IA 51579 800.869.8078

PACKAGE LABEL DISPLAY:

ENERGIQUE

SINCE 1987

HOMEOPATHIC REMEDY

JOINTOX BB

2 fl. oz. (60 ml)